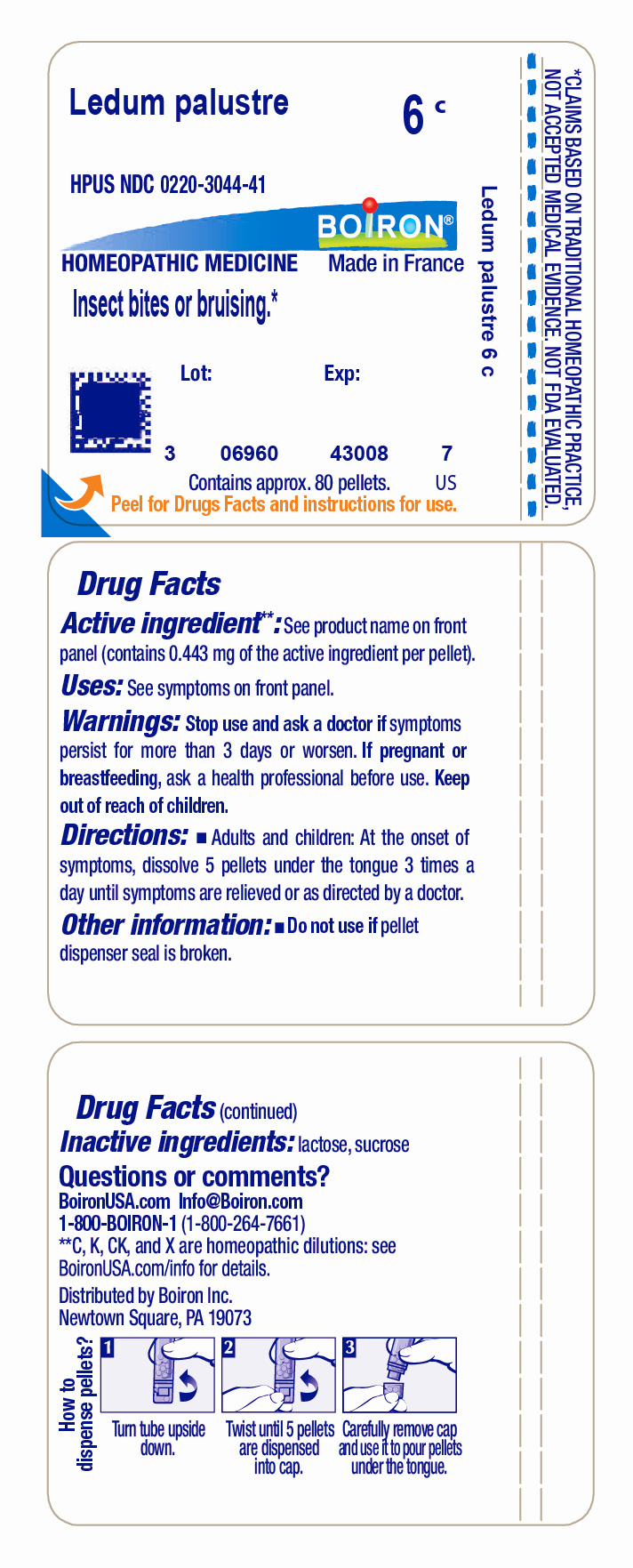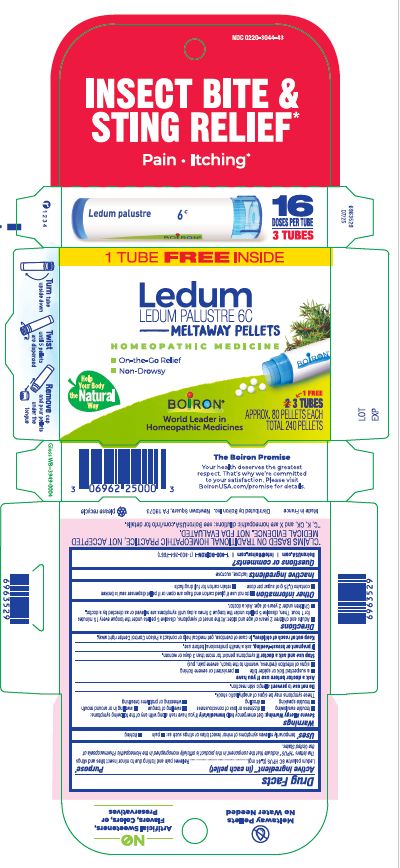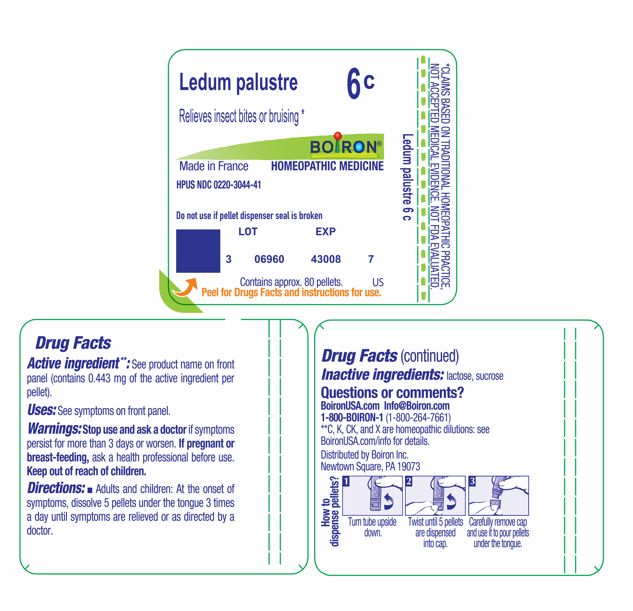 DRUG LABEL: Ledum palustre
NDC: 0220-3044 | Form: PELLET
Manufacturer: Boiron
Category: homeopathic | Type: HUMAN OTC DRUG LABEL
Date: 20260210

ACTIVE INGREDIENTS: RHODODENDRON TOMENTOSUM LEAFY TWIG 6 [hp_C]/6 [hp_C]
INACTIVE INGREDIENTS: SUCROSE; LACTOSE, UNSPECIFIED FORM

Ledum palustre 6C

Active ingredient** (in each pellet)

Ledum palustre 6C HPUS (0.44 mg)

The letters “HPUS” indicate that the component in this product is officially monographed in the Homeopathic Pharmacopoeia of the United States.

PURPOSE

Ledum palustre 6C HPUS (0.44 mg)……..Relieves pain and itching due to minor insect bites and stings

Uses*

temporarily relieves symptoms of minor insect bites or stings such as:

- pain
- itching

WARNINGS

Severe Allergy Warning: Get emergency help immediately if you have rash along with any of the following symptoms:

- trouble swallowing
- dizziness or loss of consciousness
- swelling of tongue
- swelling in or around mouth
- trouble speaking
- drooling
- wheezing or problems breathing

These symptoms may be signs of anaphylactic shock.

Do not use to prevent allergic skin reaction.

Ask a doctor before use if you have

- a suspected tick or spider bite
- persistent or severe itching
- signs of infection (redness, warmth to the touch, severe pain, pus)

Stop use and ask a doctor if symptoms persist for more than 3 days or worsen.

PREGNANCY OR BREAST FEEDING

If pregnant or breast-feeding, ask a health professional before use.

Keep out of reach of children. In case of overdose, get medical help or contact a Poison Control Center right away.

DOSAGE AND ADMINISTRATION

- Adults and children 2 years of age and older: At the onset of symptoms, dissolve 5 pellets under the tongue every 15 minutes for 1 hour. Then, dissolve 5 pellets under the tongue 3 times a day until symptoms are relieved or as directed by a doctor.
- Children under 2 years of age: Ask a doctor.

INACTIVE INGREDIENT

lactose, sucrose

QUESTIONS

BoironUSA.com

Info@Boiron.com

1-800-BOIRON-1 (1-800-264-7661)

Made in France

Distributed by Boiron Inc.

Newtown Square, PA 19073

do not use if glued carton end flaps are open or if pellet dispenser seal is broken

contains 0.25 g of sugar per dose

retain carton for full drug facts

INSECT BITE & STING RELIEF*

Pain Itching*

1 Tube

3 Tubes

APPROX. 80 PELLETS EACH

TOTAL 240 PELLETS

Turn tube upside down

Twist until 5 pellets are dispensed

Remove cap and pour under the tongue

*CLAIMS BASED ON TRADITIONAL HOMEOPATHIC PRACTICE, NOT ACCEPTED MEDICAL EVIDENCE. NOT FDA EVALUATED.
**C, K, CK, and X are homeopathic dilutions: see BoironUSA.com/info for details.